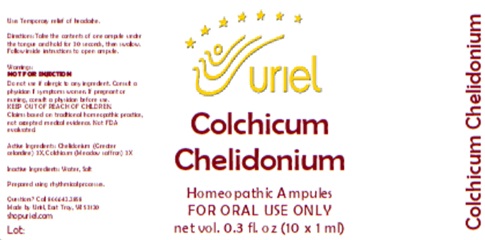 DRUG LABEL: Colchicum Chelidonium
NDC: 48951-3112 | Form: LIQUID
Manufacturer: Uriel Pharmacy Inc.
Category: homeopathic | Type: HUMAN OTC DRUG LABEL
Date: 20260116

ACTIVE INGREDIENTS: CHELIDONIUM MAJUS 3 [hp_X]/1 mL; COLCHICUM AUTUMNALE WHOLE 3 [hp_X]/1 mL
INACTIVE INGREDIENTS: WATER; SODIUM CHLORIDE

Colchicum Chelidonium

PURPOSE

Use: Temporary relief of headache.

INDICATIONS AND USAGE

FOR ORAL USE ONLY

DOSAGE AND ADMINISTRATION

Directions: Take the contents of one ampule under the tongue and hold for 30 seconds, then swallow. Follow inside instructions to open ampule.

Warnings:
Do not use if allergic to any ingredient. Consult a physician if symptoms worsen. If pregnant or nursing, consult a physician before use.
KEEP OUT OF REACH OF CHILDREN.
Claims based on traditional homeopathic practice, not accepted medical evidence. Not FDA evaluated.

KEEP OUT OF REACH OF CHILDREN.

ACTIVE INGREDIENT

Active Ingredients: Chelidonium (Greater celandine) 3X, Colchicum (Meadow saffron) 3X

Inactive Ingredients: Water, Salt

Prepared using rhythmical processes.

Questions? Call 866.642.2858

Made by Uriel, East Troy, WI 53120

shopuriel.com Lot: